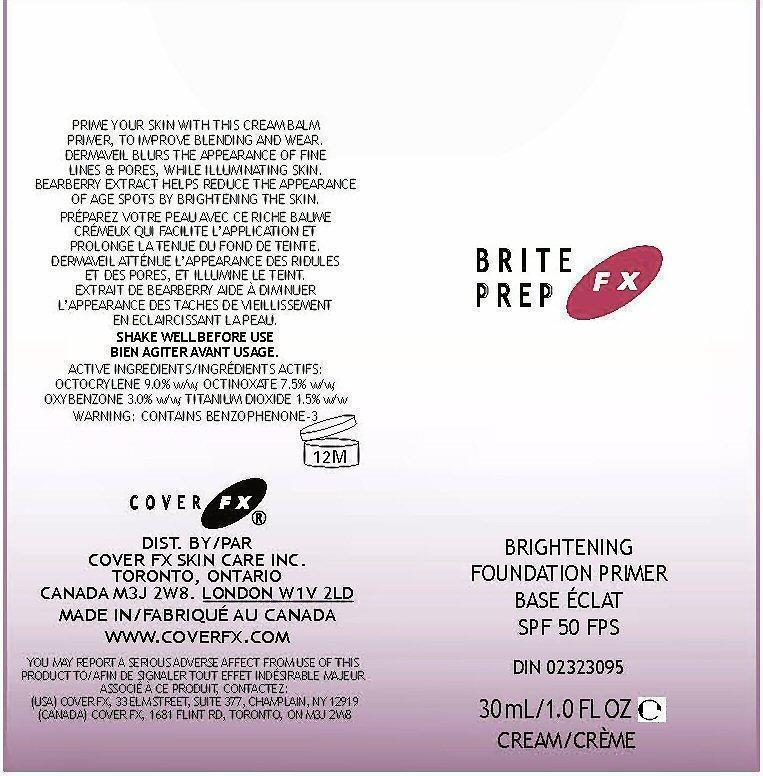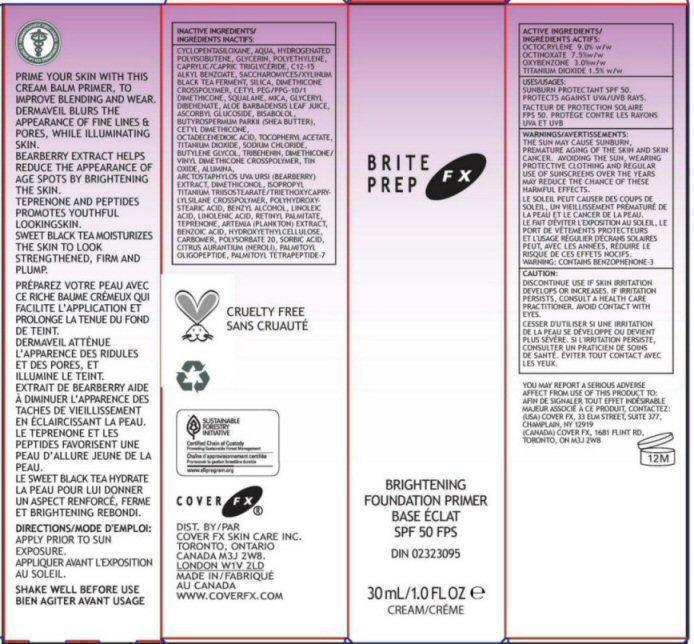 DRUG LABEL: BritePrep FX
NDC: 68327-005 | Form: CREAM
Manufacturer: Cover FX Skin Care, Inc.
Category: otc | Type: HUMAN OTC DRUG LABEL
Date: 20130219

ACTIVE INGREDIENTS: OCTOCRYLENE 9 g/100 mL; OCTINOXATE 7.5 g/100 mL; OXYBENZONE 3 g/100 mL; TITANIUM DIOXIDE 1.5 g/100 mL
INACTIVE INGREDIENTS: CYCLOMETHICONE 5; WATER; HYDROGENATED POLYBUTENE (1300 MW); GLYCERIN; HIGH DENSITY POLYETHYLENE; MEDIUM-CHAIN TRIGLYCERIDES; ALKYL (C12-15) BENZOATE; TEA LEAF; SILICON DIOXIDE; DIMETHICONE/DIENE DIMETHICONE CROSSPOLYMER; CETYL PEG/PPG-10/1 DIMETHICONE (HLB 3.7); SQUALANE; MICA; GLYCERYL 1,2-DIBEHENATE; ALOE VERA LEAF; ASCORBYL GLUCOSIDE; LEVOMENOL; SHEA BUTTER; DIMETHICONE; OCTADECENEDIOIC ACID; ALPHA-TOCOPHEROL ACETATE; TITANIUM DIOXIDE; SODIUM CHLORIDE; BUTYLENE GLYCOL; TRIBEHENIN; DIMETHICONE/VINYL DIMETHICONE CROSSPOLYMER (SOFT PARTICLE); STANNIC OXIDE; ALUMINUM OXIDE; ARCTOSTAPHYLOS UVA-URSI LEAF; ISOPROPYL TITANIUM TRIISOSTEARATE; POLYHYDROXYSTEARIC ACID (2300 MW); BENZYL ALCOHOL; LINOLEIC ACID; LINOLENIC ACID; VITAMIN A PALMITATE; TEPRENONE; BRINE SHRIMP; BENZOIC ACID; HYDROXYETHYL CELLULOSE (140 MPA.S AT 5%); CARBOMER HOMOPOLYMER TYPE C (ALLYL PENTAERYTHRITOL CROSSLINKED); POLYSORBATE 20; SORBIC ACID; CITRUS AURANTIUM FLOWER OIL; PALMITOYL OLIGOPEPTIDE; PALMITOYL TETRAPEPTIDE-7; TRIETHOXYCAPRYLYLSILANE

Active Ingredient Section

ACTIVE INGREDIENTS: OCTOCRYLENE - 9.0% w/w, OCTINOXATE 7.5% w/w, OXYBENZONE 3.0% w/w, TITANIUM DIOXIDE 1.5% w/w

Purpose Section

BRIGHTENING FOUNDATION PRIMER SPF 50

PRIME YOUR SKIN WITH THIS CREAM BALM PRIMER, TO IMPROVE BLENDING AND WEAR. DERMAVEIL BLURS THE APPEARANCE OF FINE LINES AND PORES, WHILE ILLUMINATING SKIN. BEARBERRY EXTRACT HELPS REDUCE THE APPEARANCE OF AGE SPOTS BY BRIGHTENING THE SKIN. TEPRENONE AND PEPTIDES PROMOTES YOUTHFUL LOOKINGSKIN. SWEET BLACK TEA MOISTURIZES THE SKIN TO LOOK STRENGTHENED, FIRM AND PLUMP.

Warnings Section

THE SUN MAY CAUSE SUNBURN, PREMATURE AGING OF THE SKIN AND SKIN CANCER. AVOIDING THE SUN, WEARING PROTECTIVE CLOTHING AND THE REGULAR USE OF SUNSCREENS OVER THE YEARS MAY REDUCE THE CHANCE OF THESE HARMFUL EFFECTS.

WARNINGS: CONTAINS BENZOPHENONE - 3

CAUTION: DISCONTINUE USE IF SKIN IRRITATION DEVELOPS OR INCREASES. IF IRRITATION PERSISTS, CONSULT A HEALTH CARE PRACTITIONER.

Report Section

YOU MAY REPORT A SERIOUS ADVERSE AFFECT FROM USE OF THIS PRODUCT TO (USA) COVER FX, 33 ELM STREET, SUITE 377, CHAMPLAIN, NY 12919 9CANADA) COVER FX, 1681 FLINT RD, TORONTO, ON M3J 2W8

Keep Out of Reach of Children Section

Enter section text here

Uses Section

Uses: SUNBURN PROTECTANT SPF 50. PROTECTS AGAINST UVA/UVB RAYS.

Directions Section

DIRECTIONS: APPLY PRIOR TO SUN EXPOSURE

SHAKE WELL BEFORE USE

Inactive Ingredients Section

INACTIVE INGREDIENTS: CYCLOPENTASILOXANE, AQUA, HYDROGENATED POLYISOBUTENE, GLYCERIN, POLYETHYLENE, CAPRYLIC/CAPRIC TRIGLYCERITE, C12-15 ALKYL BENZOATE, SACCHAROMYCES/XYLINUM BLACK TEA FERMENT, SILICA, DIMETHICONE CROSSPOLYMER, CETYL PEG/PPG-10/1 DIMETHICONE, SQUALANE, MICA, GLYCERYL DIBEHENATE, ALOE BARBADENSIS LEAF JUICE, ASCORBYL GLUCOSIDE, BISABOLOL, BUTYROSPERMUM PARKII (SHEA BUTTER), CETYL DIMETHICONE, OCTADCENEDIOIC ACID, TOCOPHERYL ACETATE, TITANIUM DIOXIDE, SODIUM CHLORIDE, BUTYLENE GLYCOL, TRIBEHENIN, DIMETHICONE/VINYL DIMETHICONE CROSSPOLYMER, TIN OXIDE, ALUMINA, ARCTOSTAPHYLOS UVA URSI (BEARBERRY) EXTRACT, DIMETHICONOL, ISOPROPYL TITANIUM TRIISOSTEARATE/TRIETHOXYCARYLYLSILANE CROSSPOLYMER, POLYHYDROXYSTEARIC ACID, BENZYL ALCOHOL, LINOLEIC ACID, LINOLENIC ACID, RETINYL PALMITATE, TEPRENONE, ARTEMIA (PLANKTON) EXTRACT, BENZOIC ACID, HYDROXYETHYLCELLULOSE, CARBOMER, POLYSORBATE 20, SORBIC ACID, CITRUS AURANTIUM (NEROLI), PALMITOYL OLIGOPEPTIDE, PALMITOYL TETRAPEPTIDE-7

Package Label Section

BRITE PREP FX BRIGHTENING FOUNDATION PRIMER SPF 50

30 mL/1.0 FL OZ e CREAM

DERMATOLOGISTS FIRST CHOICE

CRUELTY FREE

SUSTAINABLE FORESTRY INITIATIVE Certified Chain of Custody Promoting Sustainable Forest Management www.sfiprogram.org

COVER FX DIST. BY/ COVER FX SKIN CARE INC. TORONTO, ONTARIO CANADA M3J 2W8. LONDON W1V 2LD WWW.COVERFX.COM